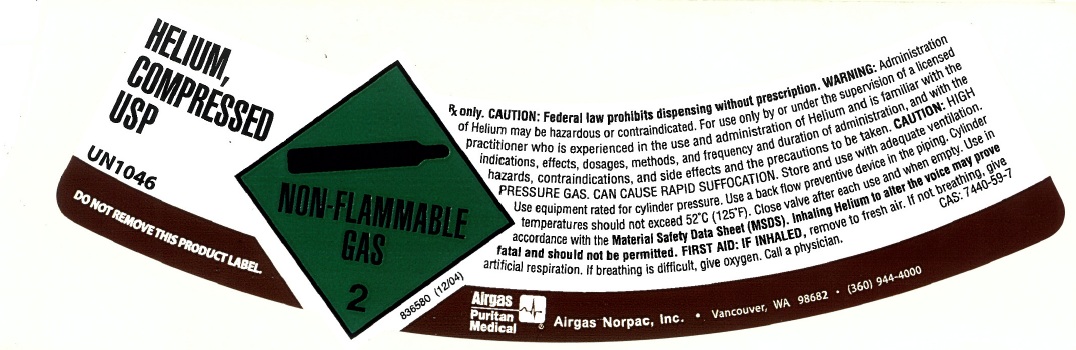 DRUG LABEL: Helium
NDC: 57472-007 | Form: GAS
Manufacturer: AIRGAS-NORPAC INC.
Category: prescription | Type: HUMAN PRESCRIPTION DRUG LABEL
Date: 20120207

ACTIVE INGREDIENTS: Helium 995 mL/1 L

Helium

PACKAGE LABEL

HELIUM, COMPRESSED USP UN1046

NON-FLAMMABLE GAS 2

DO NOT REMOVE THIS PRODUCT LABEL

Rx only. CAUTION: Federal law prohibits dispensing without prescription. WARNING: Administration of Helium may be hazardous or contraindicated. For use only by or under the supervision of a licensed practitioner who is experienced in the use and administration of Helium and is familiar with the indications, effects, dosages, methods, and frequency and duration of administration, and with the hazards, contraindications, and side effects and the precautions to be taken. CAUTION: HIGH PRESSURE GAS. CAN CAUSE RAPID SUFFOCATION. Store and use when adequate ventilation. Use equipment rated for cylinder pressure. Use a back flow preventive device in the piping. Cylinder temperatures should not exceed 52 degrees C (125 degrees F). Close valve after each use and when empty. Use in accordance with the Material Safety Data Sheet (MSDS). Inhaling Helium to alter the voice may prove fatal and should not be permitted. FIRST AID: IF INHALED, remove to fresh air. If not breathing, give artificial respiration. If breathing is difficult, give oxygen. Call a physician.

CAS: 7440-59-7

Airgas Puritan Medical

Airgas Norpac, Inc.

Vancouver, WA 98682

(360) 944-4000